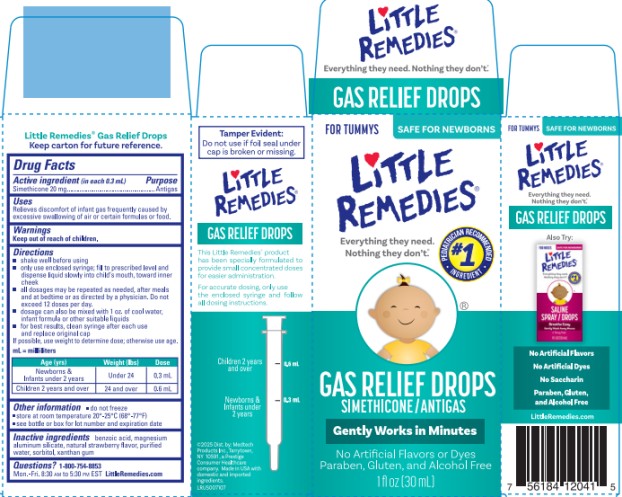 DRUG LABEL: Little Remedies
NDC: 63029-103 | Form: LIQUID
Manufacturer: Medtech Products Inc.
Category: otc | Type: HUMAN OTC DRUG LABEL
Date: 20251023

ACTIVE INGREDIENTS: DIMETHICONE 20 mg/0.3 mL
INACTIVE INGREDIENTS: CARBOXYMETHYLCELLULOSE SODIUM; MICROCRYSTALLINE CELLULOSE; CITRIC ACID MONOHYDRATE; PROPYLENE GLYCOL; WATER; SODIUM BENZOATE; SUCRALOSE; XANTHAN GUM

Little Remedies Gas Relief Drops

Drug Facts

Active ingredient (in each 0.3 mL)

Simethicone Emulsion USP 66.7 mg/ Simethicone 20 mg

Purpose

Antigas

Uses

Relieves discomfort of infant gas frequently caused by excessive swallowing of air or certain formulas or food.

Directions

- shake well before using
- only use enclosed syringe; fill to prescribed level and dispense liquid slowly into child’s mouth, toward inner cheek
- all dosages may be repeated as needed, after meals and at bedtime or as directed by a physician. Do not exceed 12 doses per day
- dosage can also be mixed with 1 fl oz of cool water, infant formula or other suitable liquids
- for best results, clean dropper after each use and replace original cap

If possible, use weight to determine dose; otherwise use age.

mL = milliliter

Age (yrs) | Weight (lbs) | Dose
Newborns & Infants under 2 | Under 24 | 0.3 mL
Children 2 and over | 24 and over | 0.6 mL

Other information

- do not freeze
- store at room temperature 20°-25°C (68°-77°F)
- see bottle or box for lot number and expiration date

Inactive ingredients

carmellose sodium (and) microcrystalline cellulose, citric acid, natural strawberry flavor, propylene glycol, purified water, sodium benzoate, sucralose, xanthan gum

Questions? 1-800-754-8853

Mon. – Fri. 8:30 am to 5:30 pm EST

LittleRemedies.com

PRINCIPAL DISPLAY PANEL

Little Remedies
Gas Relief Drops
Simethacone / Antigas
0.5 FL OZ (15 mL)